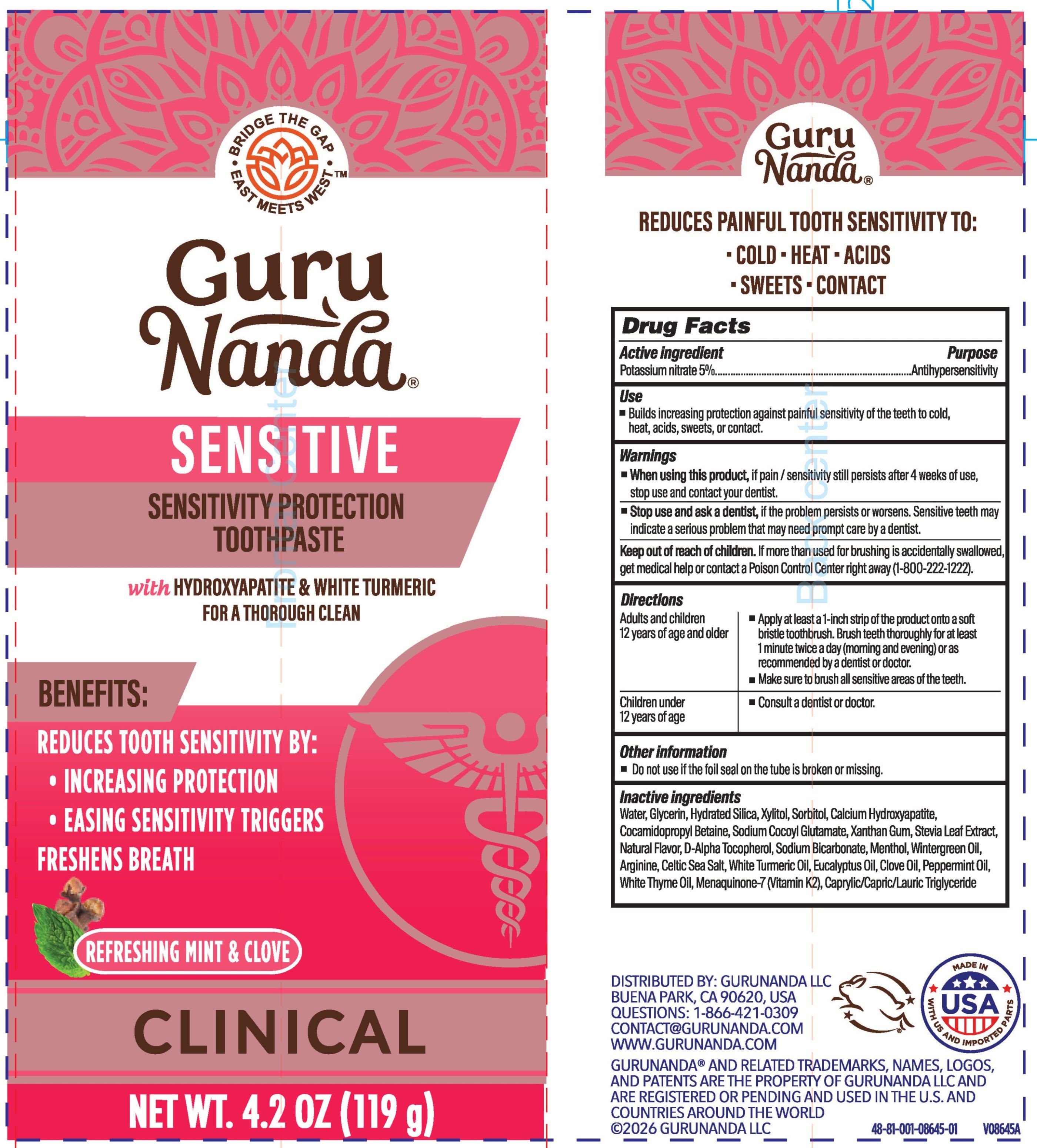 DRUG LABEL: GuruNanda Sensitive
NDC: 70708-645 | Form: PASTE
Manufacturer: GURUNANDA, LLC
Category: otc | Type: HUMAN OTC DRUG LABEL
Date: 20260119

ACTIVE INGREDIENTS: POTASSIUM NITRATE 50 mg/1 g
INACTIVE INGREDIENTS: SEA SALT; SODIUM BICARBONATE; THYME OIL; MENAQUINONE-7; XANTHAN GUM; GAULTHERIA PROCUMBENS (WINTERGREEN) LEAF OIL; HYDRATED SILICA; TURMERIC OIL; XYLITOL; SORBITOL; SODIUM COCOYL GLUTAMATE; .ALPHA.-TOCOPHEROL, D-; ARGININE; STEVIA LEAF; MENTHOL; CALCIUM HYDROXYAPATITE; EUCALYPTUS OIL; WATER; CAPRYLIC/CAPRIC/LAURIC TRIGLYCERIDE; COCAMIDOPROPYL BETAINE; GLYCERIN; CLOVE OIL; PEPPERMINT OIL

GN Sensitive Toothpaste

Active ingredient

Potassium nitrate 5%

Purpose

Antihypersensitivity

Use

Builds increasing protection against painful sensitivity of the teeth to cold, heat, acids, sweets, or contact

Warnings

When using this product

if pain/sensitivity still persists after 4 weeks of use, stop use and contact your dentist.

Stop use and ask a dentist

if the problem persists or worsens. Sensitive teeth may indicate a serious problem that may need prompt care by a dentist.

Keep out of reach of children.

If more than used for brusing is accidently swallowed, get medical help or contact a Poison Control Center right away (1-800-222-1222)

Directions

Adults and children 12 years of age and older:

- Apply at least a 1-inch strip of the product onto a soft bristle toothbrush. Brush teeth thoroughly for at least 1 minute twice a day (mroning and evening) or as recommended by a dentist or doctor.
- Make sure to brush all sensitive areas of the teeth.

Children under 12 years of age:

- Consult a dentist or doctor

Other information

Do not use if the foil seal on the tube is broken or missing

Inactive ingredients

Water, Glycerin, Hydrated Silica, Xylitol, Sorbitol, Calcium Hydroxyapatite, Cocamidopropyl Betaine, Sodium Cocoyl Glutamate, Xanthan Gum, Stevia Leaf Extract, Natural Flavor, D-Alpha Tocopherol, Sodium Bicarbonate, Menthol, Wintergreen Oil, Arginine, Celtic Sea Salt, White Turmeric Oil, Eucalyptus Oil, Clove Oil, Peppermint Oil, White Thyme Oil, Menaquinone-7 (Vitamin K2), Caprylic/Capric/Lauric Triglyceride